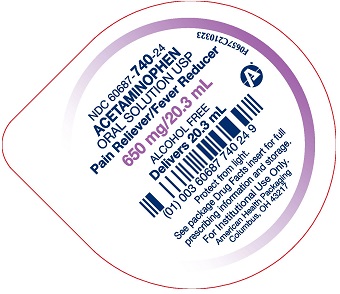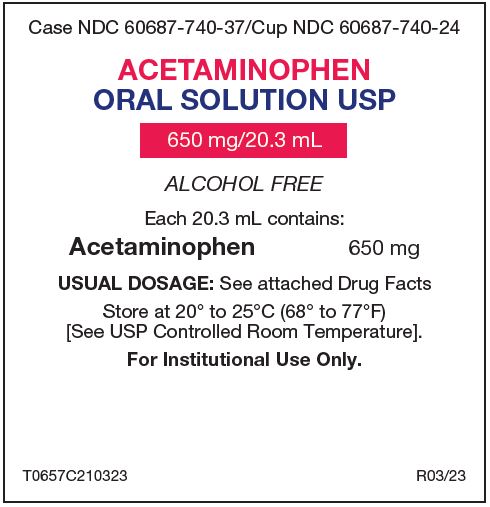 DRUG LABEL: Acetaminophen
NDC: 60687-740 | Form: SOLUTION
Manufacturer: American Health Packaging
Category: otc | Type: HUMAN OTC DRUG LABEL
Date: 20241021

ACTIVE INGREDIENTS: ACETAMINOPHEN 650 mg/20.3 mL
INACTIVE INGREDIENTS: ANHYDROUS CITRIC ACID; FD&C RED NO. 40; GLYCERIN; POLYETHYLENE GLYCOL, UNSPECIFIED; PROPYLENE GLYCOL; WATER; SODIUM BENZOATE; SODIUM CITRATE, UNSPECIFIED FORM; SORBITOL; SUCROSE

Acetaminophen Oral Solution USP
Alcohol Free

Purpose

Pain reliever/fever reducer

Active ingredient (in each 20.3 mL cup)

Acetaminophen 650 mg

Uses

temporarily relieves minor aches and pains due to:

- headache
- muscular aches
- backache
- minor pain of arthritis
- the common cold
- toothache
- premenstrual and menstrual cramps
- temporarily reduces fever

Warnings

Liver warning:

This product contains acetaminophen. Severe liver damage may occur if:

- adult takes more than 5 unit dose cups in 24 hours, which is the maximum daily amount
- taken with other drugs containing acetaminophen
- adult has 3 or more alcoholic drinks every day while using this product

Allergy alert:

Acetaminophen may cause severe skin reactions. Symptoms may include:

- skin reddening
- blisters
- rash

If a skin reaction occurs, stop use and seek medical help right away.

Sore throat warning:

If sore throat is severe, persists for more than 2 days, is accompanied or followed by fever, headache, rash, nausea, or vomiting, consult a doctor promptly.

Do not use

- with any other drug containing acetaminophen (prescription or nonprescription).
- if you are not sure whether a drug contains acetaminophen, ask a doctor or pharmacist.
- for more than 10 days for pain unless directed by a doctor
- for more than 3 days for fever unless directed by a doctor
- if you are allergic to acetaminophen or any of the inactive ingredients of this product

Ask a doctor or pharmacist before use if the user is taking the blood thinning drug warfarin.

Stop use and ask a doctor if

- symptoms do not improve
- new symptoms occur
- pain or fever persists or gets worse

PREGNANCY OR BREAST FEEDING

If pregnant or breast-feeding, ask a health professional before use.

Keep out of reach of children.

Overdose warning:

Taking more than the recommended dose (overdose) may cause liver damage. In case of overdose, get medical help or contact a Poison Control Center right away. (1-800-222-1222). Quick medical attention is critical for adults as well as children even if you do not notice any signs or symptoms.

Directions

- do not take more than directed (see overdose warning)

age | dose
adults and children 12 years of age and over | 20.3 mL (650 mg) every 4 to 6 hours not to exceed 6 doses in a 24-hour period
children under 12 years of age | consult a doctor

Other information

- Each 20.3 mL contains: sodium 8 mg
- store at 20° to 25°C (68° to 77°F). [See USP Controlled Room Temperature]
- protect from light
  a red, cherry flavored solution supplied in the following oral dosage forms:
  20.3 mL unit dose cups: 100 cups (10 x 10) NDC 60687-740-37

Inactive ingredients:

Citric acid, FD&C Red No. 40, flavoring, glycerin, polyethylene glycol, propylene glycol, purified water, sodium benzoate, sodium citrate, sorbitol and sucrose.

Questions or comments?

Call 1-800-845-8210. You may also report serious side effects to this phone number.

DO NOT USE IF SEAL IS BROKEN.

Distributed by:
American Health Packaging
Columbus, OH 43217

R03/23

Package/Label Principal Display Panel – Tray Label

Case NDC 60687-740-37/Cup NDC 60687-740-24

ACETAMINOPHEN
ORAL SOLUTION USP

650 mg/20.3 mL

ALCOHOL FREE

Each 20.3 mL contains:

Acetaminophen 650 mg

USUAL DOSAGE: See attached Drug Facts

Store at 20° to 25°C (68° to 77°F)
[See USP Controlled Room Temperature].

For Institutional Use Only.

T0657C210323 R03/23

Package/Label Principal Display Panel – Cup Label – 650 mg/20.3 mL

NDC 60687- 740-24

ACETAMINOPHEN
ORAL SOLUTION USP
Pain Reliever/Fever Reducer
650 mg / 20.3 mL

ALCOHOL FREE
Delivers 20.3 mL

Protect from light.

See package Drug Facts insert for full
prescribing information and storage.

For Institutional Use Only.

American Health Packaging
Columbus, OH 43217

F0657C210323